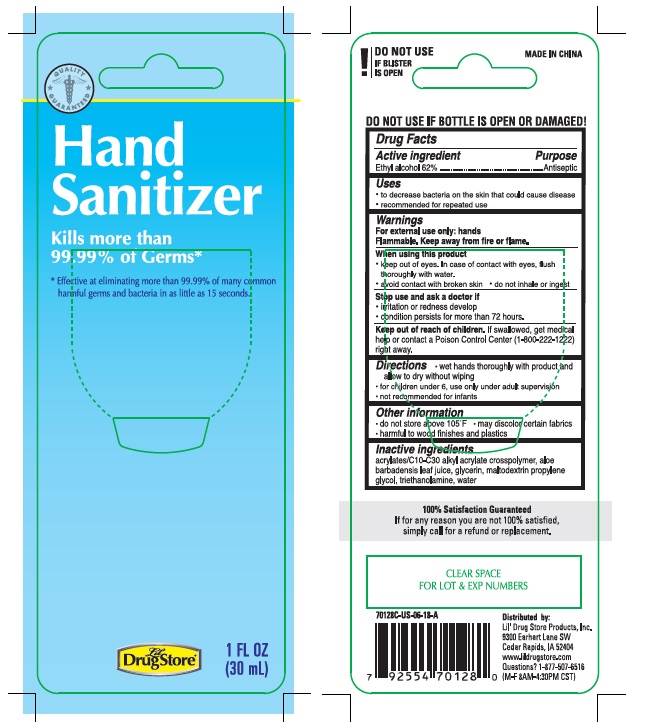 DRUG LABEL: Hand Sanitizer
NDC: 71927-008 | Form: GEL
Manufacturer: Orazen Inc
Category: otc | Type: HUMAN OTC DRUG LABEL
Date: 20250407

ACTIVE INGREDIENTS: ALCOHOL 62 mL/100 mL
INACTIVE INGREDIENTS: MALTODEXTRIN; ALOE VERA LEAF; WATER; GLYCERIN; PROPYLENE GLYCOL; CARBOMER COPOLYMER TYPE A (ALLYL PENTAERYTHRITOL CROSSLINKED); TROLAMINE

71927-008

Active ingredient:
Ethyl alcohol 62%

Purpose

Antiseptic

Warnings

For external use only: hands

Flammable. Keep away from fire and flame.

Stop use and ask a doctor if

- irritation or redness develops
- condition persists for more that 72 hours

Keep out of reach of children. If swallowed, get medical help or contact a Poison Control Center(1-800-222-1222) right away.

Directions

- wet hands thoroughly with product and allow to dry without wiping
- for children under 6, ues only under adult supervision
- not recommended for infants

Inactive ingredients

acrylates/C10-C30 alkyl acrylate crosspolymer, aloe barbadensis leaf juice, glycerin, maltodextrin, propylene glycol, triethanolamine, water

Other Information

- do not store above 105F
- may discolor some fabrics
- harmful to wood finishes and plastics

INDICATIONS AND USAGE

Uses to decrease bacteria on the skin that could cause disease. recommended for repeated use

When using this product

- keep out of eyes. In case of contact with eyes, flush thoroughly with water.
- avoid contact with broken skin
- do not inhale or ingest